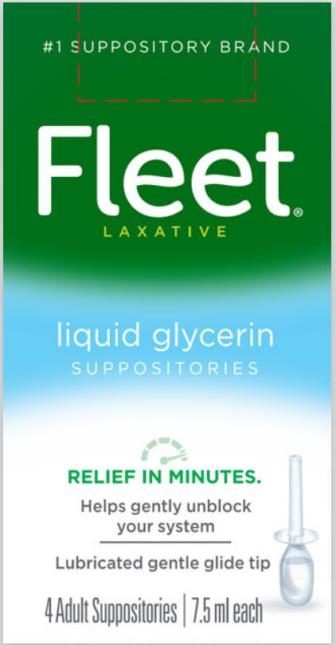 DRUG LABEL: Fleet
NDC: 0132-0185 | Form: LIQUID
Manufacturer: C.B. Fleet Company, Inc.
Category: otc | Type: HUMAN OTC DRUG LABEL
Date: 20240506

ACTIVE INGREDIENTS: GLYCERIN 5.4 g/1 1
INACTIVE INGREDIENTS: EDETATE DISODIUM; WATER

Fleet Glycerin Liquid 0132-018

Drug Facts

Active Ingredient (in each 5.4 mL average delivered dose)

Glycerin 5.4 g

Purpose

Hyperosmotic Laxative

Use

for relief of occasional constipation. This product usually produces a bowel movement in 15 minutes to 1 hour.

Warnings

May cause rectal discomfort or a burning sensation.

For rectal use only.

Ask a doctor before using any laxative if you

- have a sudden change in bowel habits lasting more than 2 weeks
- already used a laxative for more than 1 week

Stop using this product and consult a doctor if you have

- rectal bleeding
- no bowel movement within 1 hour of using this product

These symptoms may indicate a serious condition.

Keep out of reach of children.

If swallowed, get medical help or contact a Poison Control Center right away.

Directions

Single Daily Dosage (per 24 hours)

Adults and children 6 years and over 1 suppository or as directed by a doctor

Children 2 to under 6 years use Fleet® Pedia-Lax® Liquid

Children under 2 years consult a doctor

Left-side position: Lie on left side with right knee bent and arms resting comfortably.

Knee-chest position: Kneel, then lower head and chest forward until left side of face is resting on surface with left arm folded comfortably

Administering the laxative: CAUTION: REMOVE ORANGE PROTECTIVE SHIELD BEFORE INSERTING.

Hold unit upright, grasping bulb of unit with fingers. Grasp orange protective shield with other hand, pull gently to remove. With steady pressure, insert tip into rectum with a slight side-to-side movement, with tip pointing toward navel. Do not force the applicator tip into the rectum, as this can cause injury. Insertion may be easier if person receiving suppository bears down as if having a bowel movement. This helps relax the muscles around the anus. Squeeze the bulb until nearly all liquid is expelled. While continuing to squeeze the bulb, remove tip from rectum and discard unit. It is not necessary to empty unit completely. The unit contains more than the amount of liquid needed for effective use. A small amount of liquid will remain in the unit after use.

For a more detailed step-by-step instructional video on how to use Fleet® products, visit our website www.fleetlabs.com to watch the “how to use” video.

Inactive Ingredients

edetate disodium, purified water

Questions?

1-866-255-6960 or www.fleetlabs.com

PRINCIPAL DISPLAY PANEL

Fleet Laxative

Liquid Glycerin Suppositories

4Adult Suppositories

7.5 ml each